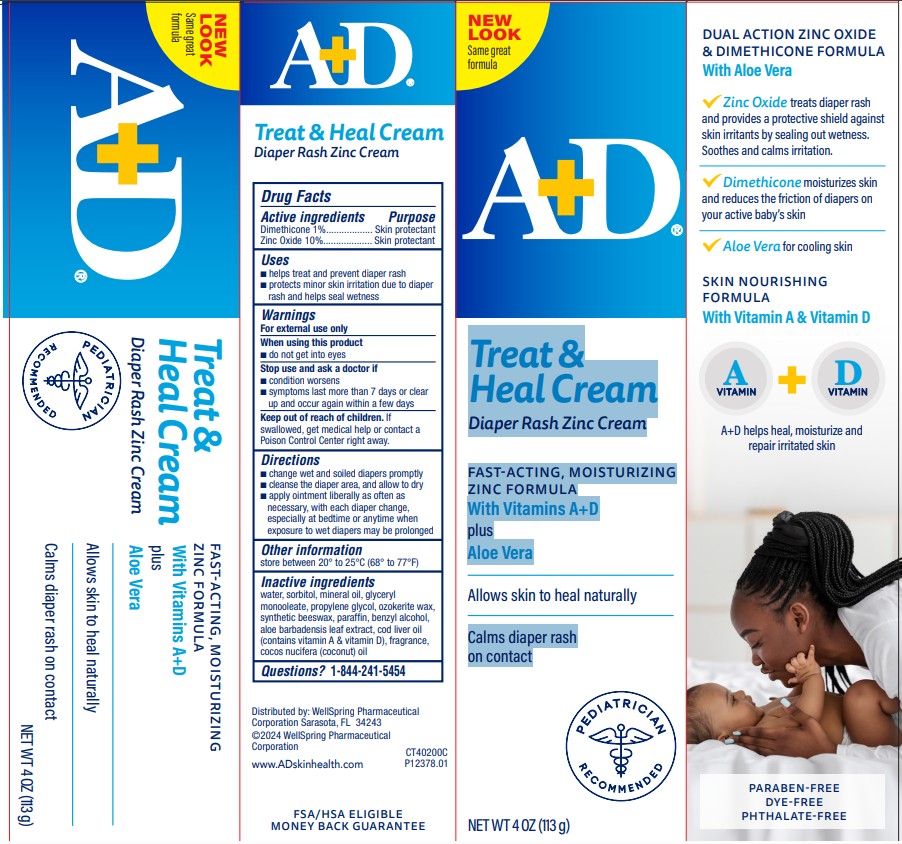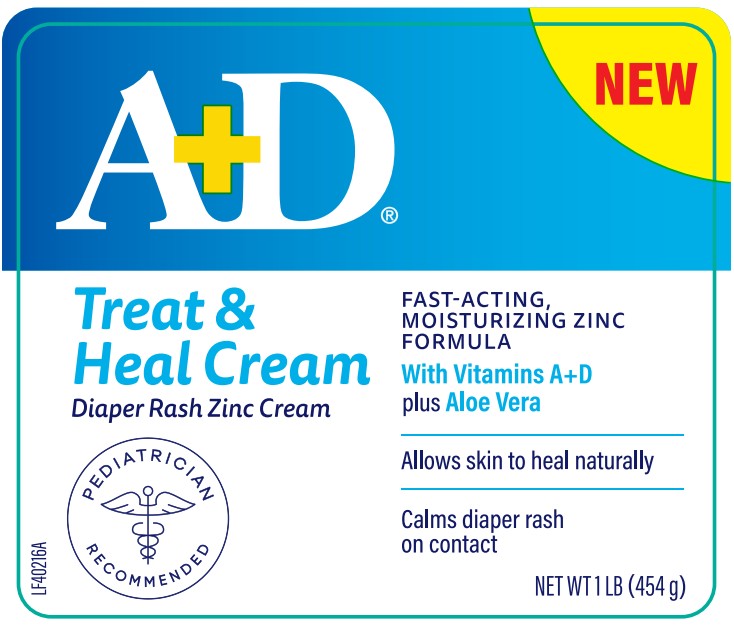 DRUG LABEL: AD Treat Diaper Rash Cream with Dimethicone and Zinc Oxide
NDC: 65197-402 | Form: CREAM
Manufacturer: WellSpring Pharmaceutical Corporation
Category: otc | Type: HUMAN OTC DRUG LABEL
Date: 20250604

ACTIVE INGREDIENTS: DIMETHICONE 1 g/100 g; ZINC OXIDE 10 g/100 g
INACTIVE INGREDIENTS: ALOE VERA LEAF; BENZYL ALCOHOL; COCONUT OIL; COD LIVER OIL; GLYCERYL MONOOLEATE; MINERAL OIL; CERESIN; PARAFFIN; PROPYLENE GLYCOL; SORBITOL; SYNTHETIC BEESWAX; WATER

A+D Treat Diaper Rash Cream with Dimethicone and Zinc Oxide

Active Ingredients

Dimethicone 1%

Zinc Oxide 10%

Purpose

Diaper Rash Cream

Diaper Rash Cream

Uses

- helps treat and prevent diaper rash
- protects minor skin irritation due to diaper rash and helps seal out wetness

Warnings

For external use only

When using this product

- do not get into eyes

Stop use and ask a doctor if

- condition worsens
- symptoms last more than 7 days or clear up and occur again within a few days

Keep out of reach of children

- If swallowed, get medical help or contact a Poison Control Center right away.

Directions

- change wet and soiled diapers promptly
- cleanse the diaper area, and allow to dry
- apply cream liberally as often as necessary, with each diaper change, especially at bedtime or anytime when exposure to wet diapers may be prolonged

Other information

store between 20° to 25°C (68° to 77°F)

Inactive ingredients

- aloe barbadensis leaf extract, benzyl alcohol, cocos nucifera (coconut) oil, cod liver oil (contains vitamin A & vitamin D), fragrance, glyceryl monooleate, light mineral oil, ozokerite, paraffin, propylene glycol, sorbitol, synthetic beeswax, water

Questions?

1-844-241-5454

Distributed by:

WellSpring Pharmaceutical Corporation
Sarasota, FL 34243

© 2023 WellSpring Pharmaceutical Corporation

www.ADskinhealth.com

PACKAGE LABEL. PRINCIPAL DISPLAY PANEL

Treat & Heal Cream Diaper Rash Zinc Cream

FAST-ACTING, MOISTURIZING ZINC FORMULA

With Vitamins A+D

plu

Aloe Vera

Allows skin to heal naturally

Calms diaper rash on contact

NET WT 4 OZ (113g)

CT40200C

A+D Treat Zinc Ointment 454g.

NET WT1 LB (454g)

LF40216A